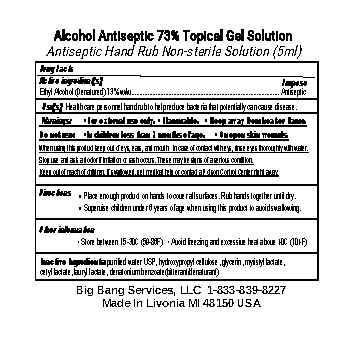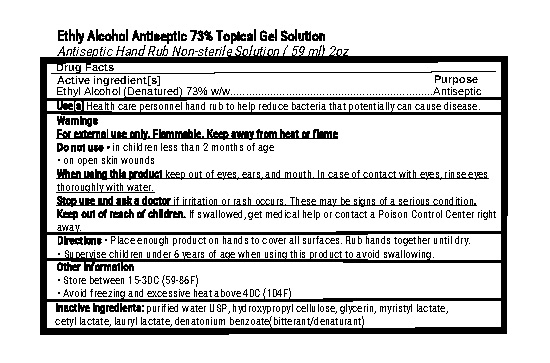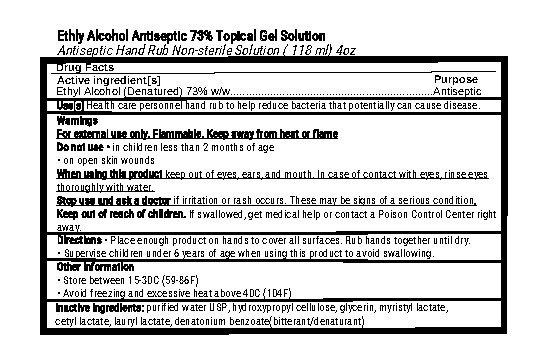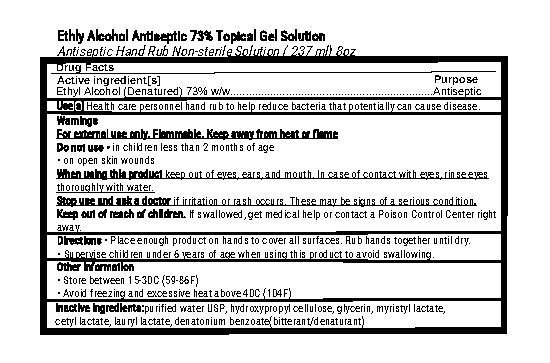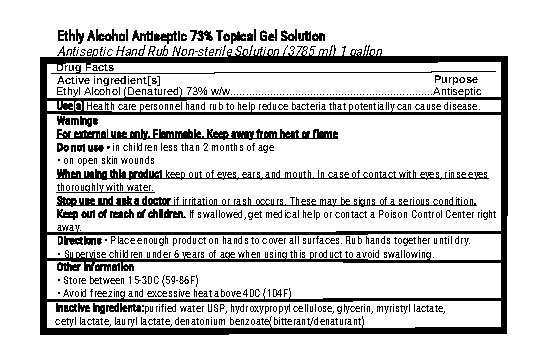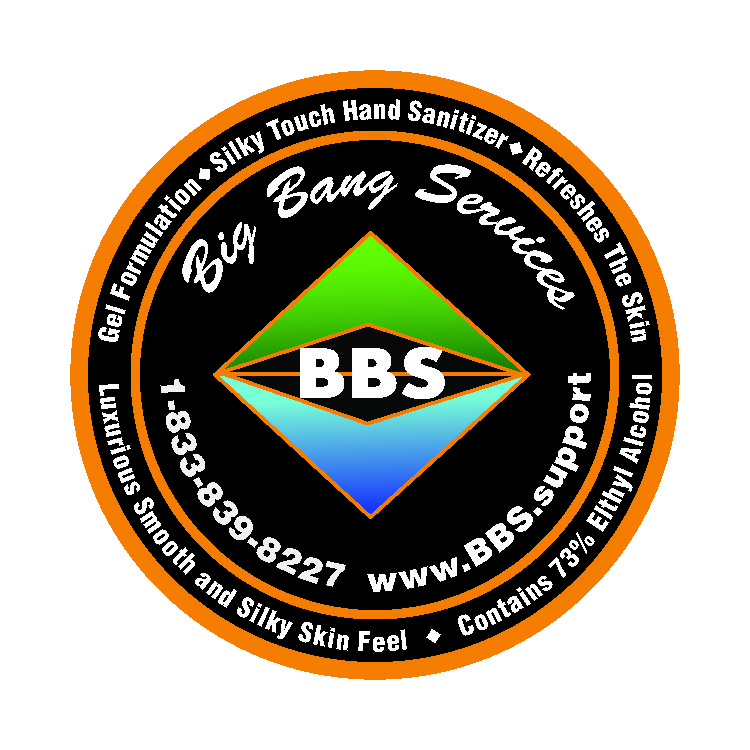 DRUG LABEL: Hand Sanitizer
NDC: 75184-003 | Form: SOLUTION
Manufacturer: Big Bang Services, L.L.C
Category: otc | Type: HUMAN OTC DRUG LABEL
Date: 20200511

ACTIVE INGREDIENTS: ALCOHOL 2391 mL/3785 mL
INACTIVE INGREDIENTS: CETYL LACTATE 0.01 mL/3785 mL; MYRISTYL LACTATE 0.05 mL/3785 mL; GLYCERIN 70 mL/3785 mL; HYDROXYPROPYL CELLULOSE (90000 WAMW) 36 mL/3785 mL; LAURYL LACTATE 0.08 mL/3785 mL; WATER 754 mL/3785 mL; DENATONIUM BENZOATE 0.02 mL/3785 mL

The hand sanitizer is manufactured using only the following United States Pharmacopoeia (USP) grade ingredients in the preparation of the product (percentage in final product formulation).

1. Alcohol (ethanol) (USP or Food Chemical Codex (FCC) grade) (73%, volume/volume (w/w)) in an aqueous solution denatured according to Alcohol and Tobacco Tax and Trade Bureau regulations in 27 CFR part 20.
2. Glycerol (1.5% w/w).

3. Hydroxypropylcellulose(Kulcel H) (1.1% w/w).

4. Ceraphyl 31 ester (1.0% w/w)

a. Lauryl Alcohol

b. Myristyl Alcohol

c. Cetyl Alcohol
5. Denatonium benzoate
6. Sterile distilled water or boiled cold water.

Active Ingredient(s)

Alcohol 73% w/w. Purpose: Antiseptic

Purpose

Antiseptic, Hand Sanitizer

Use

Hand Sanitizer to help reduce bacteria that potentially can cause disease. For use when soap and water are not available.

Warnings

For external use only. Flammable. Keep away from heat or flame

Do not use

- in children less than 2 months of age
- on open skin wounds

When using this product keep out of eyes, ears, and mouth. In case of contact with eyes, rinse eyes thoroughly with water.
Stop use and ask a doctor if irritation or rash occurs. These may be signs of a serious condition.
Keep out of reach of children. If swallowed, get medical help or contact a Poison Control Center right away.

Stop use and ask a doctor if irritation or rash occurs. These may be signs of a serious condition.

Keep out of reach of children. If swallowed, get medical help or contact Poison Control Center right away.

DOSAGE AND ADMINISTRATION

Place enough product on hands to cover all surfaces. Rub hands together until dry.

Supervise children under 6 years of age when using this product to avoid swallowing.

STORAGE AND HANDLING

Store between 15-30C (59-86F)

Avoid freezing and excessive heat above 40C (104F)

INACTIVE INGREDIENT

purified water USP, hydroxypropyl cellulose, glycerin, myristyl lactate,
cetyl lactate, lauryl lactate, denatonium benzoate(bitterant/denaturant)

PACKAGE LABEL

5 ml NDC:75184-003-01

59 ml NDC:75184-003-02

118 ml NDC:75184-003-04

237 ml NDC:75184-003-08

3785 ml NDC:75184-003-10